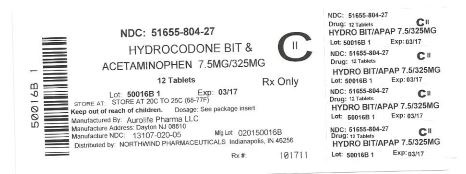 DRUG LABEL: Hydrocodone Bitartrate and Acetaminophen
NDC: 51655-804 | Form: TABLET
Manufacturer: Northwind Pharmaceuticals
Category: prescription | Type: HUMAN PRESCRIPTION DRUG LABEL
Date: 20150731
DEA Schedule: CII

ACTIVE INGREDIENTS: HYDROCODONE BITARTRATE 7.5 mg/1 1; ACETAMINOPHEN 325 mg/1 1
INACTIVE INGREDIENTS: CROSCARMELLOSE SODIUM; POVIDONE K30; STARCH, CORN; SILICON DIOXIDE; CROSPOVIDONE; MAGNESIUM STEARATE; CELLULOSE, MICROCRYSTALLINE; STEARIC ACID

Package Label.Principal Display Panel

NDC: 51655-804-27

HYDROCODONE BIT & ACETAMINOPHEN 7.5MG/325MG CII

12 Tablets

Rx Only

Lot:

Exp:

Store at 20C to 25C (68-77F)

Keep out of reach of children.

Dosage: See package insert.

Manufactured By: Aurolife Pharma LLC

Manufacture Address: Dayton, NJ 08810

Manufacture NDC: 13107-020-05

Mfg Lot: 020150016B

Distributed by: Northwind Pharmaceuticals Indianapolis, IN 46256

Rx#: